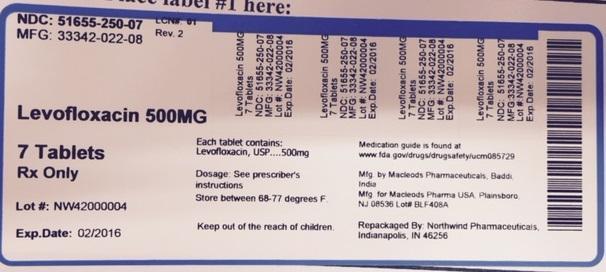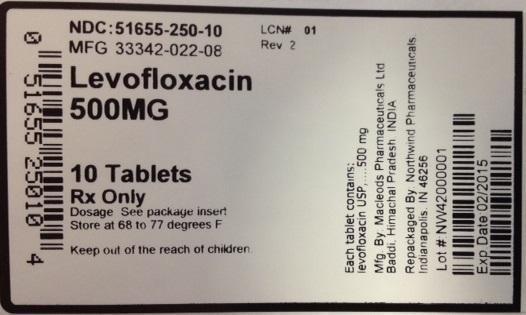 DRUG LABEL: Levofloxacin
NDC: 51655-250 | Form: TABLET, FILM COATED
Manufacturer: Northwind Pharmaceuticals
Category: prescription | Type: HUMAN PRESCRIPTION DRUG LABEL
Date: 20150120

ACTIVE INGREDIENTS: LEVOFLOXACIN 500 mg/1 1

Levofloxacin

Label Display

NDC: 51655-250-10

MFG: 33342-022-08

Levofloxacin 500 mg

10 tablets

Rx only

Dosage: See package insert

Store at 68-77 degrees F.

Keep out of the reach of children.

Each tablet contains: levofloxacin USP....500 mg

Mfg. By: Macleods Pharmaceuticals Ltd Baddi, Himachai Pradesh, India

Repackaged by Northwind Pharmaceuticals, Indianapolis, IN 46256

Lot#:

Exp Date:

NDC: 51655-250-07

MFG: 33342-022-08

Levofloxacin 500 mg

7 tablets

Rx only

Lot#

Exp. Date:

Each tablet contains: levofloxacin USP....500 mg

Dosage: See package insert

Store at 68-77 degrees F.

Keep out of the reach of children.

Medication guide is found at www.fda.gov/drugs/drugsafety/ucm085729

Mfg. By: Macleods Pharmaceuticals Ltd Baddi, Himachai Pradesh, India

Mfg. for: Macleods Pharma USA Plainsboro, NJ 08536 Lot#

Repackaged by Northwind Pharmaceuticals, Indianapolis, IN 46256

BOXED WARNING

WARNING

Fluoroquinolones, including levofloxacin, are associated with an increased risk of tendinitis and tendon rupture in all ages. This risk is further increased in older patients usually over 60 years of age, in patients taking corticosteroid drugs, and in patients with kidney, heart or lung transplants [See Warnings and Precautions (5.1)].
Fluoroquinolones, including levofloxacin, may exacerbate muscle weakness in persons with myasthenia gravis. Avoid levofloxacin in patients with a known history of myasthenia gravis [See Warnings and Precautions (5.2)].

INDICATIONS & USAGE

To reduce the development of drug-resistant bacteria and maintain the effectiveness of levofloxacin and other antibacterial drugs, levofloxacin should be used only to treat or prevent infections that are proven or strongly suspected to be caused by susceptible bacteria. When culture and susceptibility information are available, they should be considered in selecting or modifying antibacterial therapy. In the absence of such data, local epidemiology and susceptibility patterns may contribute to the empiric selection of therapy.
Levofloxacin tablets are indicated for the treatment of adults (≥18 years of age) with mild, moderate, and severe infections caused by susceptible isolates of the designated microorganisms in the conditions listed in this section.

Culture and susceptibility testing
Appropriate culture and susceptibility tests should be performed before treatment in order to isolate and identify organisms causing the infection and to determine their susceptibility to levofloxacin [see Microbiology(12.4)]. Therapy with levofloxacin may be initiated before results of these tests are known; once results become available, appropriate therapy should be selected.
As with other drugs in this class, some isolates of Pseudomonas aeruginosa may develop resistance fairly rapidly during treatment with levofloxacin. Culture and susceptibility testing performed periodically during therapy will provide information about the continued susceptibility of the pathogens to the antimicrobial agent and also the possible emergence of bacterial resistance.

1.1 Nosocomial Pneumonia

Levofloxacin is indicated for the treatment of nosocomial pneumonia due to methicillinsusceptible Staphylococcus aureus, Pseudomonas aeruginosa, Serratia marcescens, Escherichia coli, Klebsiella pneumoniae, Haemophilus influenzae, or Streptococcus pneumoniae. Adjunctive therapy should be used as clinically indicated. Where Pseudomonas aeruginosa is a documented or presumptive pathogen, combination therapy with an antipseudomonal β-lactam is recommended [see Clinical Studies (14.1)].

1.2 Community-Acquired Pneumonia: 7-14 day Treatment Regimen

Levofloxacin is indicated for the treatment of community-acquired pneumonia due to methicillin-susceptible Staphylococcus aureus, Streptococcus pneumoniae (including multidrug-resistant Streptococcus pneumoniae [MDRSP]), Haemophilus influenzae, Haemophilus parainfluenzae, Klebsiella pneumoniae, Moraxella catarrhalis, Chlamydophila pneumoniae, Legionella pneumophila, or Mycoplasma pneumoniae [see Dosage and Administration (2.1) and Clinical Studies (14.2)].

MDRSP isolates are strains resistant to two or more of the following antibacterials: penicillin (MIC ≥2 mcg/mL), 2nd generation cephalosporins, e.g., cefuroxime, macrolides, tetracyclines and trimethoprim/sulfamethoxazole.

1.3 Community-Acquired Pneumonia: 5-day Treatment Regimen

Levofloxacin is indicated for the treatment of community-acquired pneumonia due to Streptococcus pneumoniae (excluding multi-drug-resistant strains [MDRSP]), Haemophilus influenzae, Haemophilus parainfluenzae, Mycoplasma pneumoniae, or Chlamydophila pneumoniae [see Dosage and Administration (2.1)and Clinical Studies (14.3)].

1.4 Acute Bacterial Sinusitis: 5-day and 10-14 day Treatment Regimens

Levofloxacin is indicated for the treatment of acute bacterial sinusitis due to Streptococcus pneumoniae, Haemophilus influenzae, or Moraxella catarrhalis [see Clinical Studies (14.4)].

1.5 Acute Bacterial Exacerbation of Chronic Bronchitis

Levofloxacin is indicated for the treatment of acute bacterial exacerbation of chronic bronchitis due to methicillin-susceptible Staphylococcus aureus, Streptococcus pneumoniae, Haemophilus influenzae, Haemophilus parainfluenzae, or Moraxella catarrhalis.

1.6 Complicated Skin and Skin Structure Infections

Levofloxacin is indicated for the treatment of complicated skin and skin structure infections due to methicillin-susceptible Staphylococcus aureus, Enterococcus faecalis, Streptococcus pyogenes, or Proteus mirabilis [see Clinical Studies (14.5)].

1.7 Uncomplicated Skin and Skin Structure Infections

Levofloxacin is indicated for the treatment of uncomplicated skin and skin structure infections (mild to moderate) including abscesses, cellulitis, furuncles, impetigo, pyoderma, wound infections, due to methicillin-susceptible Staphylococcus aureus, or Streptococcus pyogenes.

1.8 Chronic Bacterial Prostatitis

Levofloxacin is indicated for the treatment of chronic bacterial prostatitis due to Escherichia coli, Enterococcus faecalis, or methicillin-susceptible Staphylococcus epidermidis [see Clinical Studies (14.6)].

1.9 Complicated Urinary Tract Infections: 5-day Treatment Regimen

Levofloxacin is indicated for the treatment of complicated urinary tract infections due to Escherichia coli, Klebsiella pneumoniae, or Proteus mirabilis [see Clinical Studies (14.7)].

1.10 Complicated Urinary Tract Infections: 10-day Treatment Regimen

Levofloxacin is indicated for the treatment of complicated urinary tract infections (mild to moderate) due to Enterococcus faecalis, Enterobacter cloacae, Escherichia coli, Klebsiella pneumoniae, Proteus mirabilis, or Pseudomonas aeruginosa [see Clinical Studies (14.8)].

1.11 Acute Pyelonephritis: 5 or 10-day Treatment Regimen

Levofloxacin is indicated for the treatment of acute pyelonephritis caused by Escherichia coli, including cases with concurrent bacteremia [see Clinical Studies(14.7, 14.8)].].

1.12 Uncomplicated Urinary Tract Infections

Levofloxacin is indicated for the treatment of uncomplicated urinary tract infections (mild to moderate) due to Escherichia coli, Klebsiella pneumoniae, or Staphylococcus saprophyticus.

1.13 Inhalational Anthrax (Post-Exposure)

Levofloxacin is indicated for inhalational anthrax (post-exposure) to reduce the incidence or progression of disease following exposure to aerosolized Bacillus anthracis. The effectiveness of levofloxacin is based on plasma concentrations achieved in humans, a surrogate endpoint reasonably likely to predict clinical benefit. Levofloxacin has not been tested in humans for the post-exposure prevention of inhalation anthrax. The safety of levofloxacin in adults for durations of therapy beyond 28 days or in pediatric patients for durations of therapy beyond 14 days has not been studied. Prolonged levofloxacin therapy should only be used when the benefit outweighs the risk [see Dosage and Administration(2.1, 2.2) and Clinical Studies (14.9)].

1.14 Plague

Levofloxacin is indicated for treatment of plague, including pneumonic and septicemic plague, due to Yersinia pestis (Y. pestis) and prophylaxis for plague in adults and pediatric patients, 6 months of age and older. Efficacy studies of levofloxacin could not be conducted in humans with plague for ethical and feasibility reasons. Therefore, approval of this indication was based on an efficacy study conducted in animals [seeDosage and Administration (2.1, 2.2) and Clinical Studies (14.10)].

USE IN SPECIFIC POPULATIONS

8.1 Pregnancy

Pregnancy Category C. levofloxacin was not teratogenic in rats at oral doses as high as 810 mg/kg/day which corresponds to 9.4 times the highest recommended human dose based upon relative body surface area, or at intravenous doses as high as 160 mg/kg/day corresponding to 1.9 times the highest recommended human dose based upon relative body surface area. The oral dose of 810 mg/kg/day to rats caused decreased fetal body weight and increased fetal mortality. No teratogenicity was observed when rabbits were dosed orally as high as 50 mg/kg/day which corresponds to 1.1 times the highest recommended human dose based upon relative body surface area, or when dosed intravenously as high as 25 mg/kg/day, corresponding to 0.5 times the highest recommended human dose based upon relative body surface area.

There are, however, no adequate and well-controlled studies in pregnant women. Levofloxacin should be used during pregnancy only if the potential benefit justifies the potential risk to the fetus.

8.3 Nursing Mothers

Based on data on other fluoroquinolones and very limited data on levofloxacin, it can be presumed that levofloxacin will be excreted in human milk. Because of the potential for serious adverse reactions from levofloxacin in nursing infants, a decision should be made whether to discontinue nursing or to discontinue the drug, taking into account the importance of the drug to the mother.

8.4 Pediatric Use

Quinolones, including levofloxacin, cause arthropathy and osteochondrosis in juvenile animals of several species. [see Warnings and Precautions [5.10]and Animal Toxicology and/or Pharmacology (13.2)]

Inhalational Anthrax (Post-Exposure)

Levofloxacin is indicated in pediatric patients 6 months of age and older, for inhalational anthrax (post-exposure). The risk-benefit assessment indicates that administration of levofloxacin to pediatric patients is appropriate. The safety of levofloxacin in pediatric patients treated for more than 14 days has not been studied [see Indications and Usage (1.13),Dosage and Administration (2.2) andClinical Studies (14.9)].

Plague

Levofloxacin is indicated in pediatric patients, 6 months of age and older, for treatment of plague, including pneumonic and septicemic plague due to Yersinia pestis (Y. pestis) and prophylaxis for plague. Efficacy studies of levofloxacin could not be conducted in humans with pneumonic plague for ethical and feasibility reasons. Therefore, approval of this indication was based on an efficacy study conducted in animals. The risk-benefit assessment indicates that administration of levofloxacin to pediatric patients is appropriate [see Indications and Usage (1.14), Dosage and Administration (2.2) and Clinical Studies (14.10)].

Safety and effectiveness in pediatric patients below the age of six months have not been established.

Adverse Events

In clinical trials, 1534 children (6 months to 16 years of age) were treated with oral and intravenous levofloxacin. Children 6 months to 5 years of age received levofloxacin 10 mg/kg twice a day and children greater than 5 years of age received 10 mg/kg once a day (maximum 500 mg per day) for approximately 10 days.

A subset of children in the clinical trials (1340 levofloxacin -treated and 893 non-fluoroquinolone-treated) enrolled in a prospective, long-term surveillance study to assess the incidence of protocol-defined musculoskeletal disorders (arthralgia, arthritis, tendinopathy, gait abnormality) during 60 days and 1 year following the first dose of study drug. Children treated with levofloxacin had a significantly higher incidence of musculoskeletal disorders when compared to the non-fluoroquinolone-treated children.

Arthralgia was the most frequently occurring musculoskeletal disorder in both treatment groups. Most of the musculoskeletal disorders in both groups involved multiple weight-bearing joints. Disorders were moderate in 8/46 (17%) children and mild in 35/46 (76%) levofloxacin treated children and most were treated with analgesics. The median time to resolution was 7 days for levofloxacin -treated children and 9 for non-fluoroquinolone-treated children (approximately 80% resolved within 2 months in both groups). No child had a severe or serious disorder and all musculoskeletal disorders resolved without sequelae.
Vomiting and diarrhea were the most frequently reported adverse events, occurring in similar frequency in the levofloxacin -treated and non-fluoroquinolone-treated children.
In addition to the events reported in pediatric patients in clinical trials, events reported in adults during clinical trials or post-marketing experience [see Adverse Reactions (6)] may also be expected to occur in pediatric patients.

8.5 Geriatric Use

Geriatric patients are at increased risk for developing severe tendon disorders including tendon rupture when being treated with a fluoroquinolone such as levofloxacin. This risk is further increased in patients receiving concomitant corticosteroid therapy. Tendinitis or tendon rupture can involve the Achilles, hand, shoulder, or other tendon sites and can occur during or after completion of therapy; cases occurring up to several months after fluoroquinolone treatment have been reported. Caution should be used when prescribing levofloxacin to elderly patients especially those on corticosteroids. Patients should be informed of this potential side effect and advised to discontinue levofloxacin and contact their healthcare provider if any symptoms of tendinitis or tendon rupture occur [see Boxed Warning; Warnings and Precautions (5.1); and Adverse Reactions (6.3)].

In phase 3 clinical trials, 1,945 levofloxacin -treated patients (26%) were ≥ 65 years of age. Of these, 1,081 patients (14%) were between the ages of 65 and 74 and 864 patients (12%) were 75 years or older. No overall differences in safety or effectiveness were observed between these subjects and younger subjects, but greater sensitivity of some older individuals cannot be ruled out.

Severe, and sometimes fatal, cases of hepatotoxicity have been reported post-marketing in association with levofloxacin. The majority of fatal hepatotoxicity reports occurred in patients 65 years of age or older and most were not associated with hypersensitivity. Levofloxacin should be discontinued immediately if the patient develops signs and symptoms of hepatitis [see Warnings and Precautions (5.5)].

Elderly patients may be more susceptible to drug-associated effects on the QT interval. Therefore, precaution should be taken when using levofloxacin with concomitant drugs that can result in prolongation of the QT interval (e.g., Class IA or Class III antiarrhythmics) or in patients with risk factors for torsade de pointes (e.g., known QT prolongation, uncorrected hypokalemia) [see Warnings and Precautions (5.9)].

The pharmacokinetic properties of levofloxacin in younger adults and elderly adults do not differ significantly when creatinine clearance is taken into consideration. However, since the drug is known to be substantially excreted by the kidney, the risk of toxic reactions to this drug may be greater in patients with impaired renal function. Because elderly patients are more likely to have decreased renal function, care should be taken in dose selection, and it may be useful to monitor renal function [see Clinical Pharmacology (12.3)].

8.6 Renal Impairment

Clearance of levofloxacin is substantially reduced and plasma elimination half-life is substantially prolonged in patients with impaired renal function (creatinine clearance < 50 mL/min), requiring dosage adjustment in such patients to avoid accumulation. Neither hemodialysis nor continuous ambulatory peritoneal dialysis (CAPD) is effective in removal of levofloxacin from the body, indicating that supplemental doses of levofloxacin are not required following hemodialysis or CAPD [see Dosage and Administration (2.3)].

8.7 Hepatic Impairment

Pharmacokinetic studies in hepatically impaired patients have not been conducted. Due to the limited extent of levofloxacin metabolism, the pharmacokinetics of levofloxacin are not expected to be affected by hepatic impairment.

Warnings and Precautions

Risk of tendinitis and tendon rupture is increased. This risk is further increased in older patients usually over 60 years of age, in patients taking corticosteroids, and in patients with kidney, heart or lung transplants. Discontinue if pain or inflammation in a tendon occurs. May exacerbate muscle weakness in persons with myasthenia gravis. Avoid use in patients with a known history of myasthenia gravis. Anaphylactic reactions and allergic skin reactions, serious, occasionally fatal, may occur after first dose. Hematologic (including agranulocytosis, thrombocytopenia), and renal toxicities may occur after multiple doses. Hepatotoxicity: Severe, and sometimes fatal, hepatoxicity has been reported. Discontinue immediately if signs and symptoms of hepatitis occur. Central nervous system effects, including convulsions, anxiety, confusion, depression, and insomnia may occur after the first dose. Use with caution in patients with known or suspected disorders that may predispose them to seizures or lower the seizure threshold Increased. Intracranial pressure (pseudotumor cerebri) has been reported. Clostridium difficile-associated colitis: evaluate if diarrhea occurs. Peripheral neuropathy: discontinue immediately if symptoms occur in order to prevent irreversibility. Prolongation of the QT interval and isolated cases of torsade de pointes have been reported. Avoid use in patients with known prolongation, those with hypokalemia, and with other drugs that prolong the QT interval

Contraindications

Known hypersensitivity to levofloxacin tablets or other quinolones

Adverse Reactions

The most common reactions (≥3%) were nausea, headache, diarrhea, insomnia, constipation and dizziness.

To report SUSPECTED ADVERSE REACTIONS, contact Macleods Pharma USA, Inc., at 1-888-943-3210 or FDA at 1-800-FDA-1088 or www.fda.gov/medwatch

DRUG INTERACTIONS

7.1 Chelation Agents: Antacids, Sucralfate, Metal Cations, Multivitamins

Levofloxacin Tablets

While the chelation by divalent cations is less marked than with other fluoroquinolones, concurrent administration of levofloxacin tablets with antacids containing magnesium, or aluminum, as well as sucralfate, metal cations such as iron, and multivitamin preparations with zinc may interfere with the gastrointestinal absorption of levofloxacin, resulting in systemic levels considerably lower than desired. Tablets with antacids containing magnesium, aluminum, as well as sucralfate, metal cations such as iron, and multivitamins preparations with zinc or didanosine may substantially interfere with the gastrointestinal absorption of levofloxacin, resulting in systemic levels considerably lower than desired. These agents should be taken at least two hours before or two hours after oral levofloxacin administration.

7.2 Warfarin

No significant effect of levofloxacin on the peak plasma concentrations, AUC, and other disposition parameters for R- and S- warfarin was detected in a clinical study involving healthy volunteers. Similarly, no apparent effect of warfarin on levofloxacin absorption and disposition was observed. However, there have been reports during the postmarketing experience in patients that levofloxacin enhances the effects of warfarin. Elevations of the prothrombin time in the setting of concurrent warfarin and levofloxacin use have been associated with episodes of bleeding. Prothrombin time, International Normalized Ratio (INR), or other suitable anticoagulation tests should be closely monitored if levofloxacin is administered concomitantly with warfarin. Patients should also be monitored for evidence of bleeding [see Adverse Reactions (6.3); Patient Counseling Information (17.4)].

7.3 Antidiabetic Agents

Disturbances of blood glucose, including hyperglycemia and hypoglycemia, have been reported in patients treated concomitantly with fluoroquinolones and an antidiabetic agent. Therefore, careful monitoring of blood glucose is recommended when these agents are co-administered [see Warnings and Precautions (5.11); Adverse Reactions (6.2), Patient Counseling Information (17.4)].

7.4 Non-Steroidal Anti-Inflammatory Drugs

The concomitant administration of a non-steroidal anti-inflammatory drug with a fluoroquinolone, including levofloxacin, may increase the risk of CNS stimulation and convulsive seizures [see Warnings and Precautions (5.6)].

7.5 Theophylline

No significant effect of levofloxacin on the plasma concentrations, AUC, and other disposition parameters for theophylline was detected in a clinical study involving healthy volunteers. Similarly, no apparent effect of theophylline on levofloxacin absorption and disposition was observed. However, concomitant administration of other fluoroquinolones with theophylline has resulted in prolonged elimination half-life, elevated serum theophylline levels, and a subsequent increase in the risk of theophylline-related adverse reactions in the patient population. Therefore, theophylline levels should be closely monitored and appropriate dosage adjustments made when levofloxacin is co-administered. Adverse reactions, including seizures, may occur with or without an elevation in serum theophylline levels [see Warnings and Precautions (5.6)].

7.6 Cyclosporine

No significant effect of levofloxacin on the peak plasma concentrations, AUC, and other disposition parameters for cyclosporine was detected in a clinical study involving healthy volunteers. However, elevated serum levels of cyclosporine have been reported in the patient population when co-administered with some other fluoroquinolones. Levofloxacin Cmax and ke were slightly lower while Tmax and t½ were slightly longer in the presence of cyclosporine than those observed in other studies without concomitant medication. The differences, however, are not considered to be clinically significant. Therefore, no dosage adjustment is required for levofloxacin or cyclosporine when administered concomitantly.

7.7 Digoxin

No significant effect of levofloxacin on the peak plasma concentrations, AUC, and other disposition parameters for digoxin was detected in a clinical study involving healthy volunteers. Levofloxacin absorption and disposition kinetics were similar in the presence or absence of digoxin. Therefore, no dosage adjustment for levofloxacin or digoxin is required when administered concomitantly.

7.8 Probenecid and Cimetidine

No significant effect of probenecid or cimetidine on the Cmax of levofloxacin was observed in a clinical study involving healthy volunteers. The AUC and t½of levofloxacin were higher while CL/F and CLR were lower during concomitant treatment of levofloxacin with probenecid or cimetidine compared to levofloxacin alone. However, these changes do not warrant dosage adjustment for levofloxacin when probenecid or cimetidine is co-administered.

7.9 Interactions with Laboratory or Diagnostic Testing

Some fluoroquinolones, including levofloxacin, may produce false-positive urine screening results for opiates using commercially available immunoassay kits. Confirmation of positive opiate screens by more specific methods may be necessary.

OVERDOSAGE

In the event of an acute overdosage, the stomach should be emptied. The patient should be observed and appropriate hydration maintained. Levofloxacin is not efficiently removed by hemodialysis or peritoneal dialysis.

Levofloxacin exhibits a low potential for acute toxicity. Mice, rats, dogs and monkeys exhibited the following clinical signs after receiving a single high dose oflevofloxacin: ataxia, ptosis, decreased locomotor activity, dyspnea, prostration, tremors, and convulsions. Doses in excess of 1500 mg/kg orally and 250 mg/kg IV produced significant mortality in rodents.

DESCRIPTION

Levofloxacin is a synthetic broad-spectrum antibacterial agent for oral and intravenous administration. Chemically, levofloxacin, a chiral fluorinated carboxyquinolone, is the pure (-)-(S)-enantiomer of the racemic drug substance ofloxacin. The chemical name is (--(S)-9-fluoro-2,3-dihydro-3-methyl-10-(4-methyl-1-piperazinyl)-7-oxo-7H-pyrido[1,2,3-de]-1,4-benzoxazine-6-carboxylic acid hemihydrate.

The empirical formula is C18H20FN3O4•½ H2O and the molecular weight is 370.38. Levofloxacin is a light yellowish-white to yellow-white crystal or crystalline powder. The molecule exists as a zwitterion at the pH conditions in the small intestine.

The data demonstrate that from pH 0.6 to 5.8, the solubility of levofloxacin is essentially constant (approximately 100 mg/mL). Levofloxacin is considered soluble to freely soluble in this pH range, as defined by USP nomenclature. Above pH 5.8, the solubility increases rapidly to its maximum at pH 6.7 (272 mg/mL) and is considered freely soluble in this range. Above pH 6.7, the solubility decreases and reaches a minimum value (about 50 mg/mL) at a pH of approximately 6.9.

Levofloxacin has the potential to form stable coordination compounds with many metal ions. This in vitro chelation potential has the following formation order: Al+3>Cu+2>Zn+2>Mg+2>Ca+2.

Excipients and Description of Dosage Forms

Levofloxacin Tablets

Levofloxacin Tablets are available as film-coated tablets and contain the following inactive ingredients:

250 mg (as expressed in the anhydrous form): hypromellose, crospovidone, microcrystalline cellulose, magnesium stearate, polyethylene glycol, titanium dioxide, polysorbate 80 and synthetic red iron oxide.
500 mg (as expressed in the anhydrous form): hypromellose, crospovidone, microcrystalline cellulose, magnesium stearate, polyethylene glycol, titanium dioxide, polysorbate 80 and synthetic red and yellow iron oxides.
750 mg (as expressed in the anhydrous form): hypromellose, crospovidone, microcrystalline cellulose, magnesium stearate, polyethylene glycol, titanium dioxide, polysorbate 80.

NONCLINICAL TOXICOLOGY

13.1 Carcinogenesis & Mutagenesis & Impairment Of Fertility

In a lifetime bioassay in rats, levofloxacin exhibited no carcinogenic potential following daily dietary administration for 2 years; the highest dose (100 mg/kg/day) was 1.4 times the highest recommended human dose (750 mg) based upon relative body surface area. Levofloxacin did not shorten the time to tumor development of UV-induced skin tumors in hairless albino (Skh-1) mice at any levofloxacin dose level and was therefore not photo-carcinogenic under conditions of this study. Dermal levofloxacin concentrations in the hairless mice ranged from 25 to 42 mcg/g at the highest levofloxacin dose level (300 mg/kg/day) used in the photo-carcinogenicity study. By comparison, dermal levofloxacin concentrations in human subjects receiving 750 mg of levofloxacin averaged approximately 11.8 mcg/g at Cmax.

Levofloxacin was not mutagenic in the following assays: Ames bacterial mutation assay (S. typhimurium and E. coli), CHO/HGPRT forward mutation assay, mouse micronucleus test, mouse dominant lethal test, rat unscheduled DNA synthesis assay, and the mouse sister chromatid exchange assay. It was positive in the in vitro chromosomal aberration (CHL cell line) and sister chromatid exchange (CHL/IU cell line) assays.

Levofloxacin caused no impairment of fertility or reproductive performance in rats at oral doses as high as 360 mg/kg/day, corresponding to 4.2 times the highest recommended human dose based upon relative body surface area and intravenous doses as high as 100 mg/kg/day, corresponding to 1.2 times the highest recommended human dose based upon relative body surface area.

13.2 Animal Pharmacology & or Toxicology

Levofloxacin and other quinolones have been shown to cause arthropathy in immature animals of most species tested [see Warnings and Precautions (5.10)]. In immature dogs (4–5 months old), oral doses of 10 mg/kg/day for 7 days and intravenous doses of 4 mg/kg/day for 14 days of levofloxacin resulted in arthropathic lesions. Administration at oral doses of 300 mg/kg/day for 7 days and intravenous doses of 60 mg/kg/day for 4 weeks produced arthropathy in juvenile rats. Three-month old beagle dogs dosed orally with levofloxacin at 40 mg/kg/day exhibited clinically severe arthrotoxicity resulting in the termination of dosing at Day 8 of a 14-day dosing routine. Slight musculoskeletal clinical effects, in the absence of gross pathological or histopathological effects, resulted from the lowest dose level of 2.5 mg/kg/day (approximately 0.2-fold the pediatric dose based upon AUC comparisons). Synovitis and articular cartilage lesions were observed at the 10 and 40 mg/kg dose levels (approximately 0.7-fold and 2.4-fold the pediatric dose, respectively, based on AUC comparisons). Articular cartilage gross pathology and histopathology persisted to the end of the 18-week recovery period for those dogs from the 10 and 40 mg/kg/day dose levels.

When tested in a mouse ear swelling bioassay, levofloxacin exhibited phototoxicity similar in magnitude to ofloxacin, but less phototoxicity than other quinolones.

While crystalluria has been observed in some intravenous rat studies, urinary crystals are not formed in the bladder, being present only after micturition and are not associated with nephrotoxicity.

In mice, the CNS stimulatory effect of quinolones is enhanced by concomitant administration of non-steroidal anti-inflammatory drugs.

In dogs, levofloxacin administered at 6 mg/kg or higher by rapid intravenous injection produced hypotensive effects. These effects were considered to be related to histamine release.

In vitro and in vivo studies in animals indicate that levofloxacin is neither an enzyme inducer nor inhibitor in the human therapeutic plasma concentration range; therefore, no drug metabolizing enzyme-related interactions with other drugs or agents are anticipated.